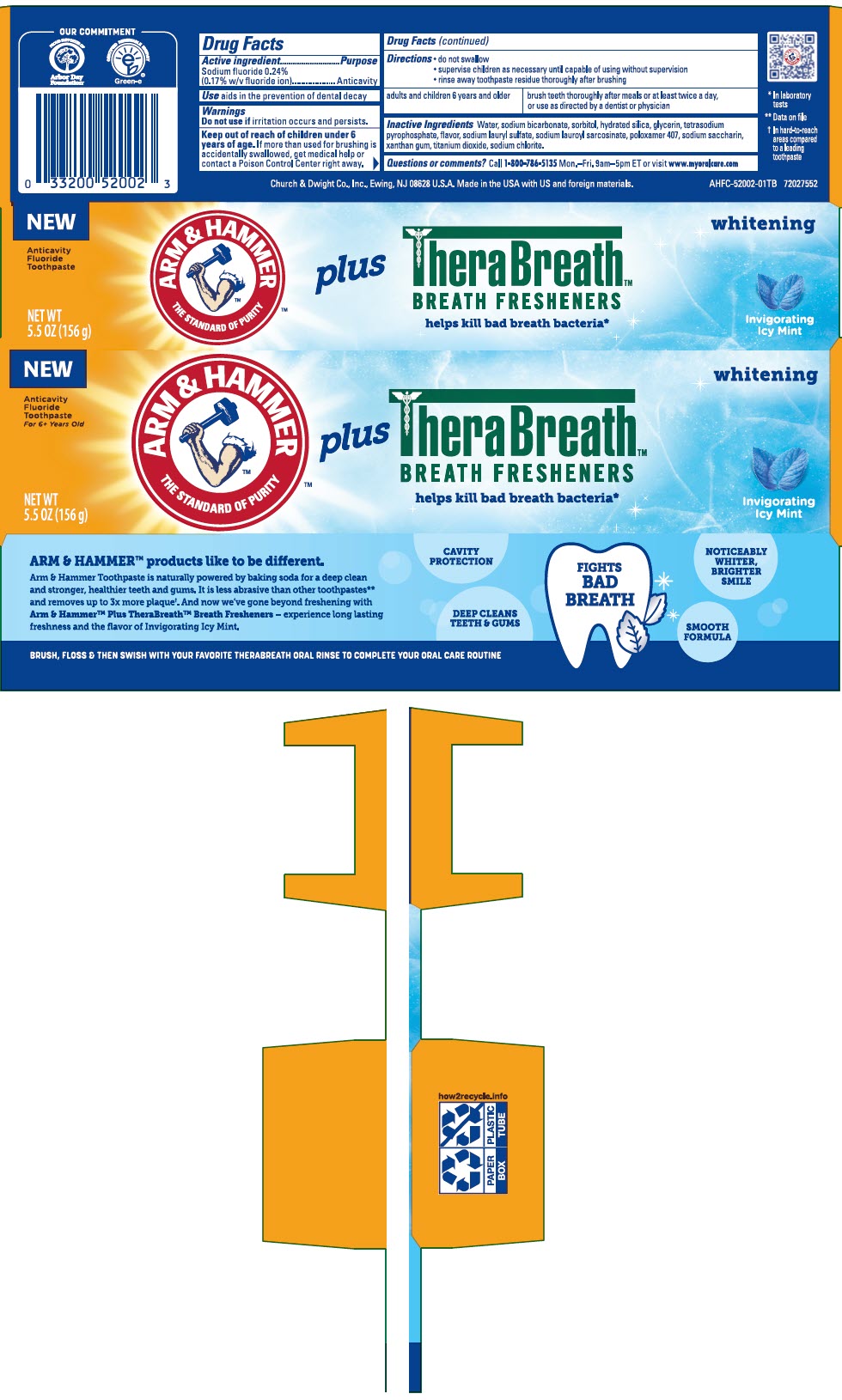 DRUG LABEL: A and H Plus Therabreath Breath Freshners
NDC: 10237-676 | Form: PASTE, DENTIFRICE
Manufacturer: Church & Dwight Co., Inc.
Category: otc | Type: HUMAN OTC DRUG LABEL
Date: 20250219

ACTIVE INGREDIENTS: SODIUM FLUORIDE 0.243 g/100 g
INACTIVE INGREDIENTS: WATER; SODIUM BICARBONATE; SORBITOL; HYDRATED SILICA; GLYCERIN; SODIUM PYROPHOSPHATE; SODIUM LAURYL SULFATE; SODIUM LAURYL SARCOSINATE; POLOXAMER 407; SACCHARIN SODIUM; XANTHAN GUM; TITANIUM DIOXIDE; SODIUM CHLORITE

A and H Plus TheraBreath™Breath Freshners Toothpaste

Drug Facts

Active ingredient

Sodium fluoride 0.24% (0.17% w/v fluoride ion)

Purpose

Anticavity

Use

aids in the prevention of dental decay

Warnings

Do not use ifirritation occurs and persists.

Keep out of reach of children under 6 years of age.If more than used for brushing is accidentally swallowed, get medical help or contact a Poison Control Center right away.

Directions

- do not swallow
- supervise children as necessary until capable of using without supervision
- rinse away toothpaste residue thoroughly after brushing

adults and children 6 years and older

brush teeth thoroughly after meals or at least twice a day, or use as directed by a dentist or physician

Inactive Ingredients

Water, sodium bicarbonate, sorbitol, hydrated silica, glycerin, tetrasodium pyrophosphate, flavor, sodium lauryl sulfate, sodium lauroyl sarcosinate, poloxamer 407, sodium saccharin, xanthan gum, titanium dioxide, sodium chlorite.

Questions or comments?

Call 1-800-786-5135Mon.–Fri. 9am–5pm ET or visit www.myoralcare.com

PRINCIPAL DISPLAY PANEL - 156 g Tube Carton

NEW

Anticavity
Fluoride
Toothpaste

ARM & HAMMER
THE STANDARD OF PURITY

plus

TheraBreath™
BREATH FRESHENERS

helps kill bad breath bacteria*

whitening

Invigorating
Icy Mint

NET WT
5.5 OZ (156 g)